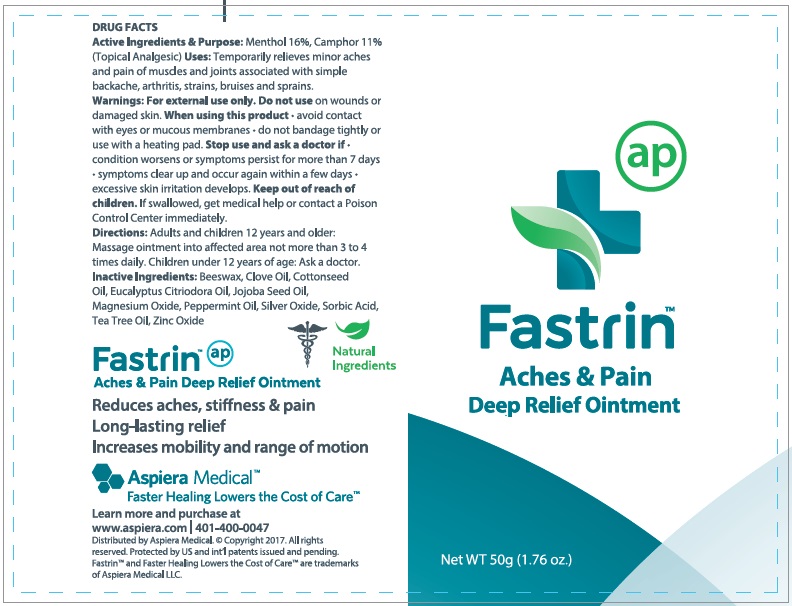 DRUG LABEL: Fastrin Aches and Pain Deep Relief
NDC: 24909-604 | Form: OINTMENT
Manufacturer: Aidance Skincare & Topical Solutions, LLC
Category: otc | Type: HUMAN OTC DRUG LABEL
Date: 20170601

ACTIVE INGREDIENTS: MENTHOL 16 g/100 g; CAMPHOR (SYNTHETIC) 11 g/100 g
INACTIVE INGREDIENTS: CLOVE OIL; CORYMBIA CITRIODORA LEAF OIL; COTTONSEED OIL; JOJOBA OIL; MAGNESIUM OXIDE; PEPPERMINT OIL; SILVER OXIDE; SORBIC ACID; TEA TREE OIL; WHITE WAX; ZINC OXIDE

Drug Facts

Active Ingredients

Menthol 16%, Camphor 11%

Purpose

Topical Analgesic

Uses

Temporarily relieves minor aches and pains of muscles and joints associated with simple backache, arthritis, strains, bruises and sprains

Warnings

For external use only. Do not use on wounds or damaged skin. When using this product - avoid contact with eyes or mucous membranes - do not bandage tightly or use with heating pad. Stop use and ask a doctor if - condition worsens or symptoms persist for more than 7 days - symptoms clear up and occur again within a few days - excessive skin irritation develops.

Keep out of reach of children.

If swallowed, get medical help or contact a Poison Control Center immediately.

Directions

Adults and children 12 years and older: Massage ointment into affected area not more than 3 to 4 times daily. Children under 12 years of age: Ask a doctor.

Inactive Ingredients

Beeswax, Clove Oil, Cottonseed Oil, Eucalyptus Citriodora Oil, Jojoba Seed Oil, Magnesium Oxide, Peppermint Oil, Silver Oxide, Sorbic Acid, Tea Tree Oil, Zinc Oxide

PRINCIPAL DISPLAY PANEL - 50g Tube

Fastrin

Aches & Pain

Deep Relief Ointment

Net WT 50g (1.76 oz.)